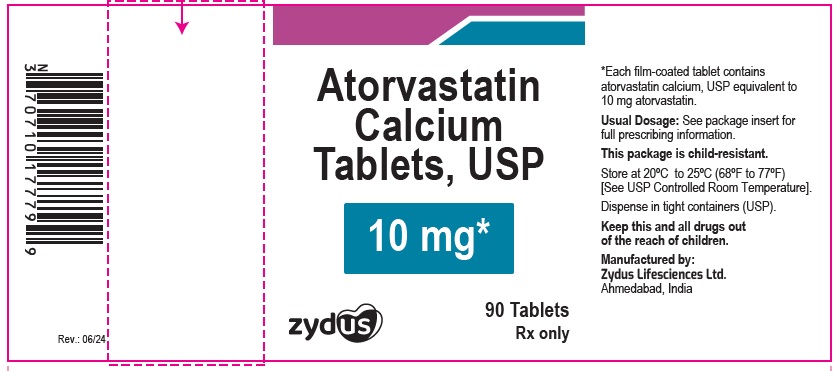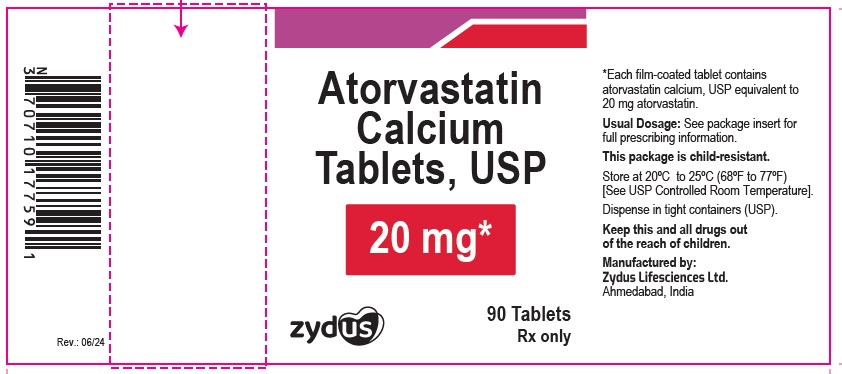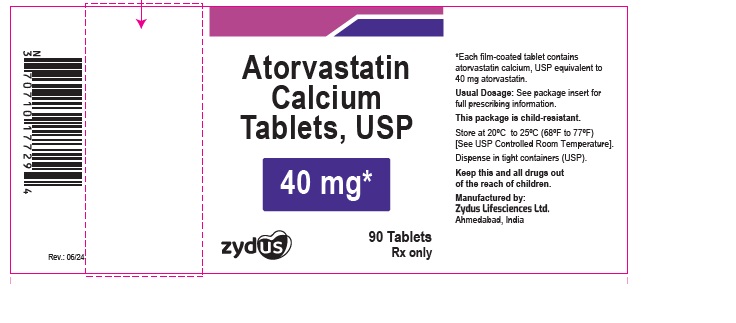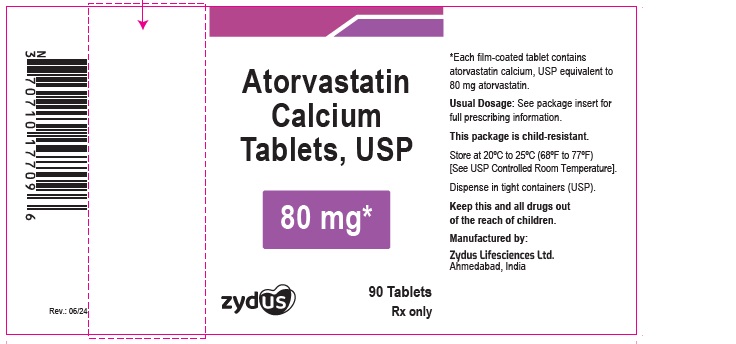 DRUG LABEL: atorvastatin calcium
NDC: 70771-1875 | Form: TABLET
Manufacturer: Zydus Lifesciences Limited
Category: prescription | Type: HUMAN PRESCRIPTION DRUG LABEL
Date: 20250530

ACTIVE INGREDIENTS: ATORVASTATIN CALCIUM TRIHYDRATE 10 mg/1 1
INACTIVE INGREDIENTS: CALCIUM CARBONATE; CROSCARMELLOSE SODIUM; HYDROXYPROPYL CELLULOSE, UNSPECIFIED; HYPROMELLOSES; LACTOSE MONOHYDRATE; MAGNESIUM STEARATE; CELLULOSE, MICROCRYSTALLINE; POLYETHYLENE GLYCOL, UNSPECIFIED; POLYSORBATE 80; TITANIUM DIOXIDE; TALC

ATORVASTATIN CALCIUM tablets, for oral use

PACKAGE LABEL

NDC 70771-1875-9

Atorvastatin Calcium Tablets, USP 10 mg

Rx Only

90 Tablets

NDC 70771-1876-9

Atorvastatin Calcium Tablets, USP 20 mg

Rx Only

90 Tablets

NDC 70771-1877-9

Atorvastatin Calcium Tablets, USP 40 mg

Rx Only

90 Tablets

NDC 70771-1878-9

Atorvastatin Calcium Tablets, USP 80 mg

Rx Only

90 Tablets